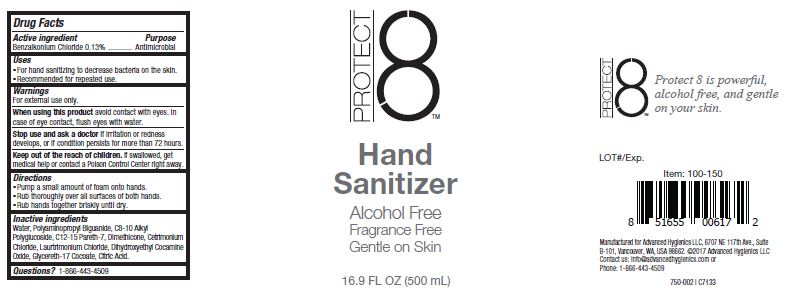 DRUG LABEL: PROTECT 8
NDC: 63002-003 | Form: LIQUID
Manufacturer: Advanced Hygienics LLC
Category: otc | Type: HUMAN OTC DRUG LABEL
Date: 20190730

ACTIVE INGREDIENTS: BENZALKONIUM CHLORIDE 1.3 g/1 mL
INACTIVE INGREDIENTS: WATER; POLIHEXANIDE; CAPRYLYL GLUCOSIDE; C12-15 PARETH-7; DIMETHICONE; CETRIMONIUM CHLORIDE; LAURTRIMONIUM CHLORIDE; DIHYDROXYETHYL COCAMINE OXIDE; GLYCERETH-17 COCOATE; CITRIC ACID MONOHYDRATE

Drug Facts

Active ingredient

Benzalkonium Chloride 0.13%

Purpose

Antimicrobial

Uses

For hand sanitizing to decrease bacteria on the skin.

Recommended for repeated use.

Warnings

For external use only.

When using this product avoid contact with eyes.

In case of eye contact, flush eyes with water.

Stop use and ask a doctor if irritation or redness develops, or if condition persists for more than 72 hours.

Keep out of the reach of children.

If swallowed, get medical help or contact a Poison Control Center right away.

Directions

Pump a small amount of foam onto hands.

Rub thoroughly over all surfaces of both hands.

Rub hands together briskly until dry.

Inactive ingredients

Water, Polyaminopropyl Biguanide, C8-10 Alkyl Polyglucoside, C12-15 Pareth-7, Dimethicone, Cetrimonium Chloride, Laurtrimonium Chloride, Dihydroxyethyl Cocamine Oxide, Glycereth-17 Cocoate, Citric acid.

PACKAGE LABEL

PROTECT 8

Hand

Sanitizer

Alcohol Free

Fragrance Free

Gentle on Skin

16.9 FL OZ (500mL)

container label2